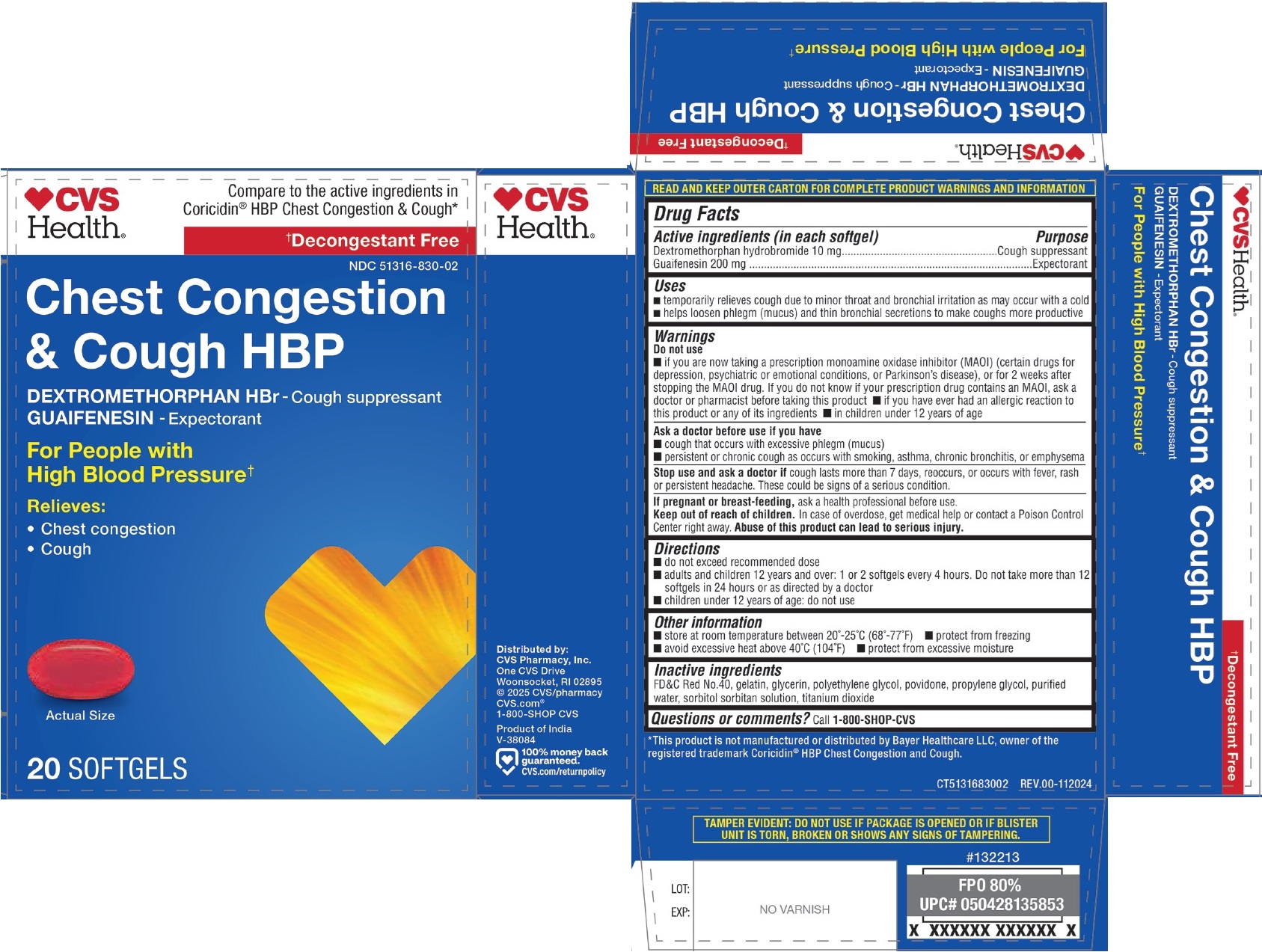 DRUG LABEL: CVS Health Chest Congestion and Cough HBP SOFTGEL
NDC: 51316-830 | Form: CAPSULE, LIQUID FILLED
Manufacturer: CVS Pharmacy, Inc
Category: otc | Type: HUMAN OTC DRUG LABEL
Date: 20250114

ACTIVE INGREDIENTS: DEXTROMETHORPHAN HYDROBROMIDE 10 mg/1 1; GUAIFENESIN 200 mg/1 1
INACTIVE INGREDIENTS: FD&C RED NO. 40; GELATIN, UNSPECIFIED; GLYCERIN; POLYETHYLENE GLYCOL, UNSPECIFIED; POVIDONE, UNSPECIFIED; PROPYLENE GLYCOL; WATER; SORBITOL; SORBITAN; TITANIUM DIOXIDE

CVS Health® Chest Congestion & Cough HBP SOFTGELS

Active ingredients (in each softgel)

Dextromethorphan hydrobromide 10 mg
Guaifenesin 200 mg

Purpose

Cough suppressant
Expectorant

Uses

• temporarily relieves cough due to minor throat and bronchial irritation as may occur with a cold
• helps loosen phlegm (mucus) and thin bronchial secretions to make coughs more productive

Warnings

Do not use
• if you are now taking a prescription monoamine oxidase inhibitor (MAOI) (certain drugs for depression, psychiatric or emotional conditions, or Parkinson's disease), or for 2 weeks after stopping the MAOI drug. If you do not know if your prescription drug contains an MAOI, ask a doctor or pharmacist before taking this product • if you have ever had an allergic reaction to this product or any of its ingredients • in children under 12 years of age

Ask a doctor before use if you have
• cough that occurs with excessive phlegm (mucus)
• persistent or chronic cough as occurs with smoking, asthma, chronic bronchitis, or emphysema

Stop use and ask a doctor if cough lasts more than 7 days, reoccurs, or occurs with fever, rash or persistent headache. These could be signs of a serious condition.

If pregnant or breast-feeding, ask a health professional before use.

Keep out of reach of children. In case of overdose, get medical help or contact a Poison Control Center right away. Abuse of this product can lead to serious injury.

Directions

• do not exceed recommended dose
• adults and children 12 years and over: 1 or 2 softgels every 4 hours. Do not take more than 12 softgels in 24 hours or as directed by a doctor
• children under 12 years of age: do not use

Other information

• store at room temperature between 20°-25°C (68°-77°F) • protect from freezing
• avoid excessive heat above 40°C (104°F) • protect from excessive moisture

Inactive ingredients

FD&C Red No.40, gelatin, glycerin, polyethylene glycol, povidone, propylene glycol, purified water, sorbitol sorbitan solution, titanium dioxide

Questions or comments?

Call 1-800-SHOP-CVS

Compare to the active ingredients in Coricidin® HBP Chest Congestion & Cough*

†Decongestant Free

For People with High Blood Pressure†

Relieves:
• Chest congestion
• Cough

READ AND KEEP OUTER CARTON FOR COMPLETE PRODUCT WARNINGS AND INFORMATION

*This product is not manufactured or distributed by Bayer Healthcare LLC, owner of the registered trademark Coricidin® HBP Chest Congestion and Cough.

Distributed by:
CVS Pharmacy, Inc.
One CVS Drive
Woonsocket, RI 02895
© 2025 CVS/pharmacy
CVS.com®

Product of India

100% money back guaranteed.
CVS.com/returnpolicy

TAMPER EVIDENT: DO NOT USE IF PACKAGE IS OPENED OR IF BLISTER UNIT IS TORN, BROKEN OR SHOWS ANY SIGNS OF TAMPERING.